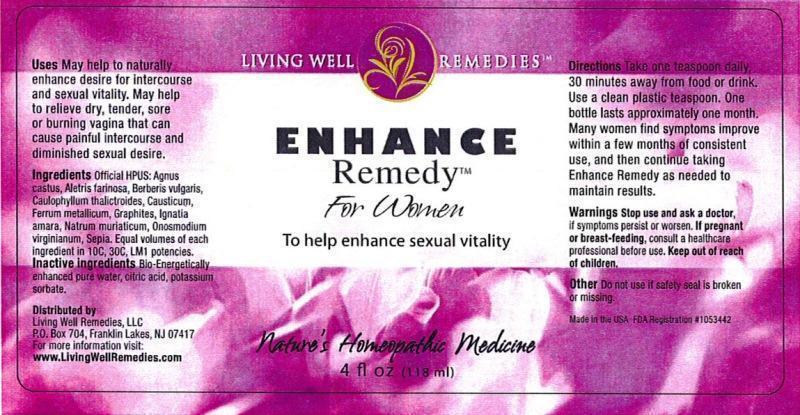 DRUG LABEL: Enhance Remedy For Women
NDC: 53852-0007 | Form: LIQUID
Manufacturer: Living Well Remedies, LLC
Category: homeopathic | Type: HUMAN OTC DRUG LABEL
Date: 20140417

ACTIVE INGREDIENTS: CHASTE TREE 10 [hp_C]/118 mL; ALETRIS FARINOSA ROOT 10 [hp_C]/118 mL; BERBERIS VULGARIS ROOT BARK 10 [hp_C]/118 mL; CAULOPHYLLUM THALICTROIDES ROOT 10 [hp_C]/118 mL; CAUSTICUM 10 [hp_C]/118 mL; IRON 10 [hp_C]/118 mL; GRAPHITE 10 [hp_C]/118 mL; STRYCHNOS IGNATII SEED 10 [hp_C]/118 mL; SODIUM CHLORIDE 10 [hp_C]/118 mL; ONOSMODIUM VIRGINIANUM WHOLE 10 [hp_C]/118 mL; SEPIA OFFICINALIS JUICE 10 [hp_C]/118 mL
INACTIVE INGREDIENTS: WATER; CITRIC ACID MONOHYDRATE; POTASSIUM SORBATE

ENHANCE Remedy™ For Women

DOSAGE AND ADMINISTRATION

Directions: Take one teaspoon daily, 30 minutes away from food or drink. Use a clean plastic teaspoon. One bottle lasts approximately one month. Many women find symptoms improve within a few months of consistent use, and then continue taking Enhance Remedy as needed to maintain results.

WARNINGS

Warnings: Stop use and ask a doctor, if symptoms persist or worsen. If pregnant or breast-feeding, consult a healthcare professional before use.

Keep out of reach of children.

OTHER SAFETY INFORMATION

Other: Do not use if safety seal is broken or missing.

PURPOSE

Uses: May help to naturally enhance desire for intercourse and sexual vitality. May help to relieve dry, tender, sore or burning vagina that can cause painful intercourse and diminished sexual desire.

ACTIVE INGREDIENT

Ingredients: Official HPUS: Agnus castus, Aletris farinosa, Berberis vulgaris, Caulophyllum thalictroides, Causticum, Ferrum metallicum, Graphites, Ignatia amara, Natrum muriaticum, Onosmodium virginianum, Sepia. Equal volumes of each ingredient in 10C, 30C, LM1 potencies.

INACTIVE INGREDIENT

Inactive ingredients: Bio-Energetically enhanced pure water, citric acid, potassium sorbate.

INDICATIONS AND USAGE

Uses: May help to naturally enhance desire for intercourse and sexual vitality. May help to relieve dry, tender, sore or burning vagina that can cause painful intercourse and diminished sexual desire.

PACKAGE LABEL

Distributed by

Living Well Remedies, LLC

P.O. Box 704,

Franklin Lakes, NJ 07417

For more information vist:

www.LivingWellRemedies.com